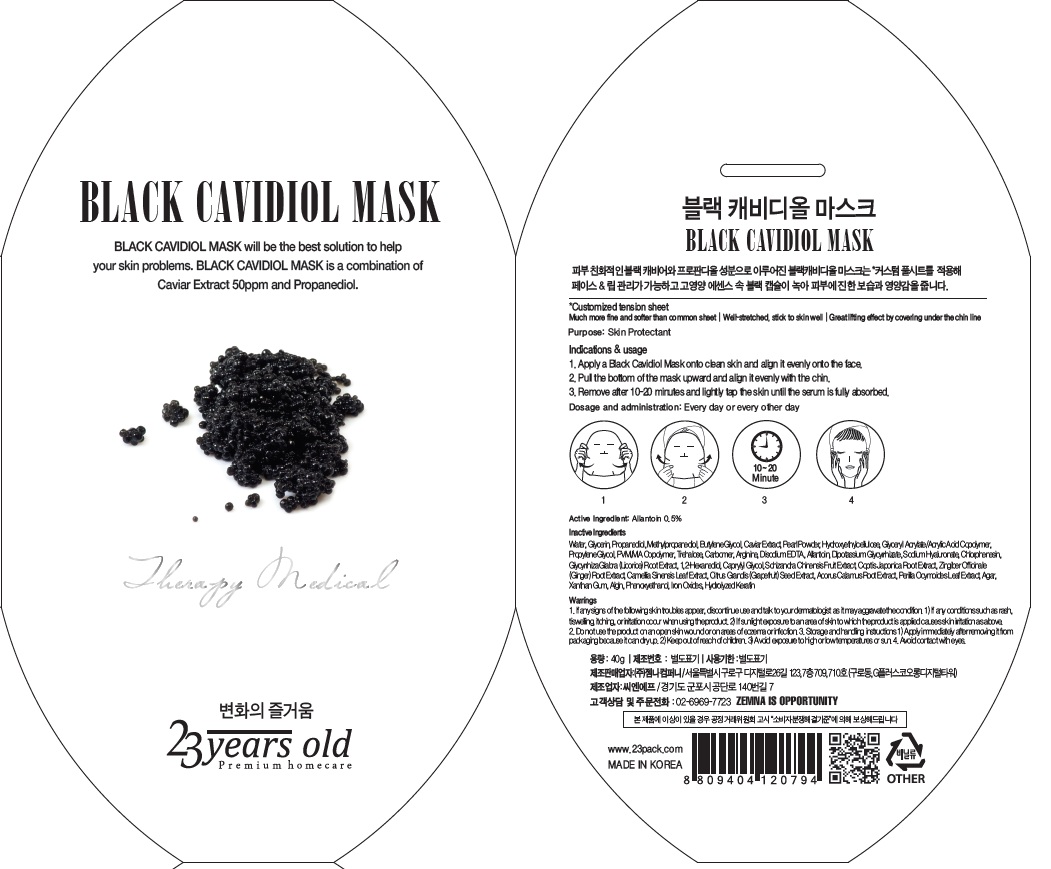 DRUG LABEL: BLACK CAVIDIOL MASK
NDC: 70768-010 | Form: PATCH
Manufacturer: ZEMNA COMPANY CO., Ltd
Category: otc | Type: HUMAN OTC DRUG LABEL
Date: 20160624

ACTIVE INGREDIENTS: Allantoin 0.2 g/40 g
INACTIVE INGREDIENTS: Water; Glycerin

ACTIVE INGREDIENT

Active Ingredient: Allantoin 0.5%

INACTIVE INGREDIENT

Inactive Ingredients: Water, Glycerin, Propanediol, Methylpropanediol, Butylene Glycol, Caviar Extract, Pearl Powder, Hydroxyethylcellulose, Glyceryl Acrylate/Acrylic Acid Copolymer, Propylene Glycol, PVM/MA Copolymer, Trehalose, Carbomer, Arginine, Disodium EDTA, Allantoin, Dipotassium Glycyrrhizate, Sodium Hyaluronate, Chlorphenesin, Glycyrrhiza Glabra (Licorice) Root Extract, 1,2-Hexanediol, Caprylyl Glycol, Schizandra Chinensis Fruit Extract, Coptis Japonica Root Extract, Zingiber Officinale (Ginger) Root Extract, Camellia Sinensis Leaf Extract, Citrus Grandis (Grapefruit) Seed Extract, Acorus Calamus Root Extract, Perilla Ocymoides Leaf Extract, Agar, Xanthan Gum, Algin, Phenoxyethanol, Iron Oxides, Hydrolyzed Keratin

PURPOSE

Purpose: Skin Protectant

WARNINGS

Warnings: 1. If any signs of the following skin troubles appear, discontinue use and talk to your dermatologist as it may aggravate the condition. 1) If any conditions such as rash, swelling, itching, or irritation occur when using the product. 2) If sunlight exposure to an area of skin to which the product is applied causes skin irritation as above. 2. Do not use the product on an open skin wound or on areas of eczema or infection. 3. Storage and handling instructions 1) Apply immediately after removing it from packaging because it can dry up. 2) Keep out of reach of children. 3) Avoid exposure to high or low temperatures or sun. 4. Avoid contact with eyes. In case of contact with eyes, rinse immediately with water.

KEEP OUT OF REACH OF CHILDREN

INDICATIONS & USAGE

Indications & usage: 1) Apply a Black Cavidiol Mask onto clean skin and align it evenly onto the face. 2) Pull the bottom of the mask upward and align it evenly with the chin. 3) Remove after 10-20 minutes and lightly tap the skin until the serum is fully absorbed.

DOSAGE & ADMINISTRATION

Dosage and administration: Every day or every other day